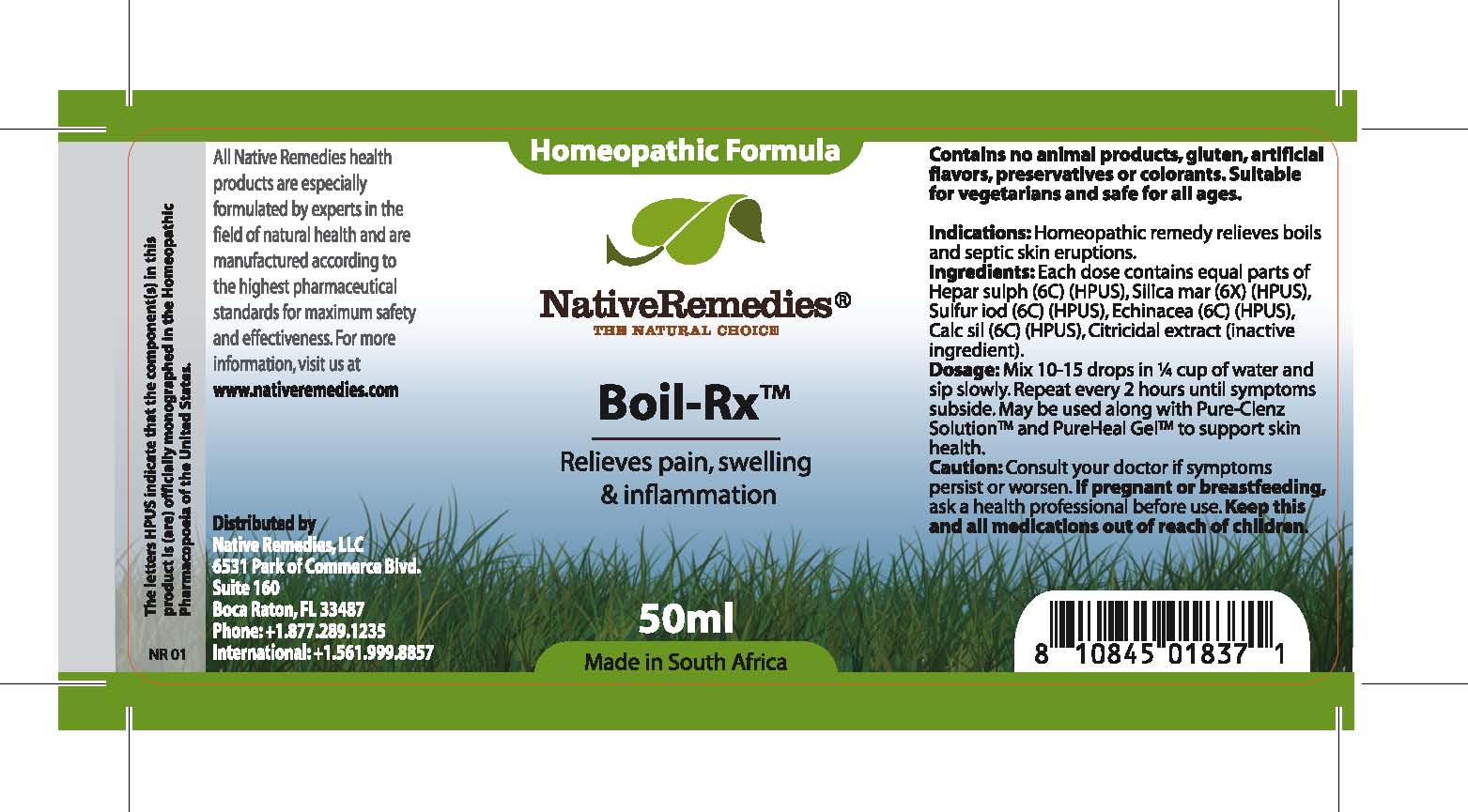 DRUG LABEL: Boil-Rx
NDC: 68647-203 | Form: TINCTURE
Manufacturer: Feelgood Health
Category: homeopathic | Type: HUMAN OTC DRUG LABEL
Date: 20100816

ACTIVE INGREDIENTS: CALCIUM SULFIDE 6 [hp_C]/40 mL; SILICON DIOXIDE 6 [hp_X]/40 mL; SULFUR IODIDE 6 [hp_C]/40 mL; ECHINACEA 6 [hp_C]/40 mL; CALCIUM SILICATE 6 [hp_C]/40 mL
INACTIVE INGREDIENTS: CITRUS PARADISI SEED 0.03 mL/50 mL; WATER 98.97 mL/50 mL

BOIL-RX

PURPOSE

Relieves pain, swelling and inflammation

INDICATIONS AND USAGE

Indications: Homeopathic remedy relieves boils and septic skin eruptions.

DOSAGE AND ADMINISTRATION

Dosage: Mix 10-15 drops in ¼ cup of water and sip slowly. Repeat every 2 hours until symptoms subside. May be used along with Pure-Clenz Solution™ and PureHeal Gel™ to support skin health.

GENERAL PRECAUTIONS

Caution: Consult your doctor if symptoms persist or worsen. Keep this and all medications out of reach of children.

ACTIVE INGREDIENT

Ingredients: Each dose contains equal parts of Hepar sulph (6C) (HPUS), Silica mar (6X) (HPUS), Sulfur iod (6C) (HPUS), Echinacea (6C) (HPUS), Calc sil (6C) (HPUS)

Citricidal Extract (inactive ingredient).

PREGNANCY

If pregnant or breastfeeding, ask a health professional before use.

WARNINGS

Contains no animal products, gluten, artificial flavors, preservatives or colorants. Suitable for vegetarians and safe for all ages.

PATIENT COUNSELING INFORMATION

All Native Remedies health products are especially formulated by experts in the field of natural health and are manufactured according to the highest pharmaceutical standards for maximum safety and effectiveness. For more information, visit us at www.nativeremedies.com

Distributed by

Native Remedies, LLC

6531 Park of Commerce Blvd.

Suite 160

Boca Raton, FL 33487

Phone: 1.877.289.1235

International: + 1.561.999.8857

The letters HPUS indicate that the component(s) in this product is (are) officially monographed in the Homeopathic Pharmacopoeia of the United States.

KEEP OUT OF REACH OF CHILDREN

Keep this and all medications out of reach of children.